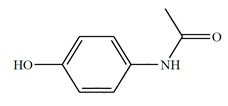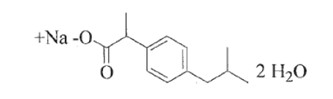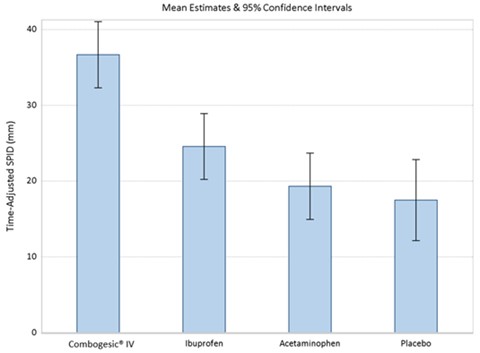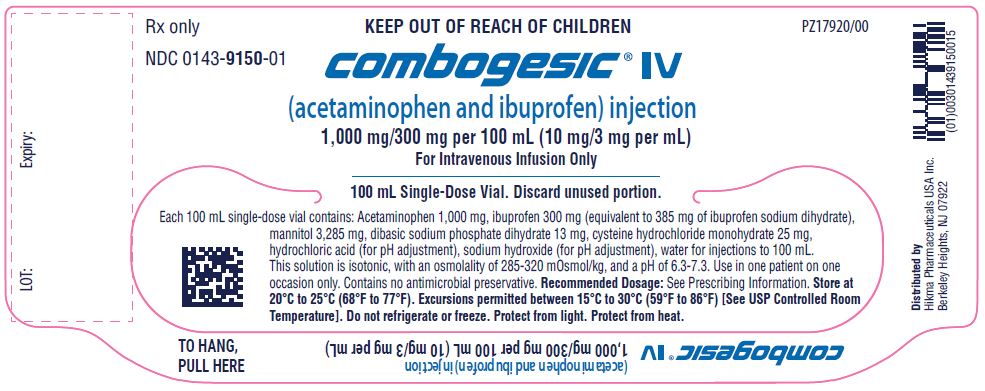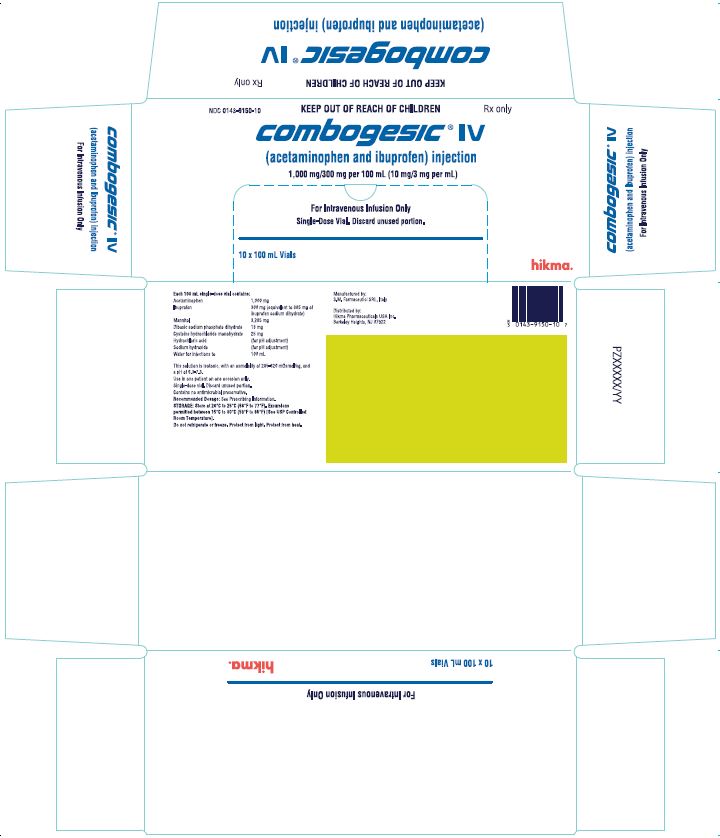 DRUG LABEL: COMBOGESIC IV
NDC: 0143-9150 | Form: INJECTION
Manufacturer: Hikma Pharmaceuticals USA Inc.
Category: prescription | Type: HUMAN PRESCRIPTION DRUG LABEL
Date: 20241125

ACTIVE INGREDIENTS: ACETAMINOPHEN 1000 mg/100 mL; IBUPROFEN 300 mg/100 mL
INACTIVE INGREDIENTS: MANNITOL 3285 mg/100 mL; SODIUM PHOSPHATE DIBASIC DIHYDRATE 13 mg/100 mL; CYSTEINE HYDROCHLORIDE 25 mg/100 mL; HYDROCHLORIC ACID; SODIUM HYDROXIDE; WATER

HIGHLIGHTS OF PRESCRIBING INFORMATION

These highlights do not include all the information needed to use COMBOGESIC IV® safely and effectively. See full prescribing information for COMBOGESIC IV.
COMBOGESIC IV (acetaminophen and ibuprofen) injection for intravenous use
Initial U.S. Approval: 2023

BOXED WARNING

WARNING: HEPATOTOXICITY, CARDIOVASCULAR RISK, and GASTROINTESTINAL RISK
See full prescribing information for complete boxed warning.
• Take care when prescribing, preparing, and administering COMBOGESIC IV to avoid dosing errors which could result in accidental overdose and death. (5.1)
• COMBOGESIC IV contains acetaminophen, which has been associated with cases of acute liver failure, at times resulting in liver transplant and death. Most of the cases of liver injury are associated with doses of acetaminophen that exceed 4000 mg per day, and often involve more than one acetaminophen-containing product. (5.2)
• Nonsteroidal anti-inflammatory drugs (NSAIDS), like the ibuprofen in COMBOGESIC IV, may cause an increased risk of serious cardiovascular thrombotic events, including myocardial infarction and stroke, which can be fatal. This risk may occur early in treatment and may increase with duration of use. (5.3).
• COMBOGESIC IV is contraindicated in the setting of coronary artery bypass graft (CABG) surgery. (4, 5.3)
• NSAIDS, like the ibuprofen in COMBOGESIC IV, cause an increased risk of serious gastrointestinal (GI) adverse events, including bleeding, ulceration, and perforation of the stomach or intestines, which can be fatal. These events can occur at any time during use and without warning symptoms. Elderly patients and patients with a prior history of peptic ulcer disease and/or GI bleeding are at greater risk for serious GI events. (5.4)

RECENT MAJOR CHANGES

Warnings and Precautions (5.10) 11/2024

1 INDICATIONS AND USAGE

COMBOGESIC IV is indicated in adults where an intravenous route of administration is considered clinically
necessary for:
• the relief of mild to moderate pain
• the management of moderate to severe pain as an adjunct to opioid analgesics

Limitations of Use
COMBOGESIC IV is indicated for short-term use of five days or less.

2 DOSAGE AND ADMINISTRATION

• Use the lowest effective dosage for the shortest duration consistent with individual patient treatment goals. (2.1).
• Do not exceed the maximum total daily dose of COMBOGESIC IV (4,000 mg acetaminophen and 1,200 mg ibuprofen) in 24 hours. (2.1)
• Do not exceed a total daily dose of 4,000 mg (4 g) of acetaminophen from all sources. (2.1)
• Do not administer with other acetaminophen-containing products. (2.1)
• For adult patients weighing greater than or equal to 50 kg (actual body weight): The recommended dosage is 1,000 mg of acetaminophen and 300 mg of ibuprofen administered as a 15-minute infusion, every 6 hours, as necessary (2.2).
• For adult patients weighing less than 50 kg (actual body weight): The recommended dosage is 15 mg/kg acetaminophen and 4.5 mg/kg ibuprofen administered as a 15-minute infusion, every 6 hours, as necessary. (2.2)

3 DOSAGE FORMS AND STRENGTHS

Injection: 1,000 mg/100 mL (10 mg/mL) of acetaminophen and 300 mg/100 mL (3 mg/mL) of ibuprofen in single-dose vial. (3)

4 CONTRAINDICATIONS

COMBOGESIC IV is contraindicated in:
• patients who have previously demonstrated hypersensitivity to acetaminophen, ibuprofen, other NSAIDs or to any of the excipients in the IV formulation (4)
• patients who have experienced asthma, urticaria, or allergic-type reactions after taking aspirin or other NSAIDs. Severe, sometimes fatal, anaphylactic reactions to NSAIDs have been reported in such patients (4, 5.9, 5.11)
• the setting of coronary artery bypass graft (CABG) surgery (4, 5.3)
• patients with severe hepatic impairment or severe active liver disease (4)

5 WARNINGS AND PRECAUTIONS

• Hypertension: Patients taking some antihypertensive medications may have impaired response to these therapies when taking NSAIDs. Monitor blood pressure. (5.5)
• Heart Failure and Edema: Avoid use of COMBOGESIC IV in patients with severe heart failure unless benefits are expected to outweigh risk of worsening heart failure. (5.6)
• Renal Toxicity: Long-term administration of NSAIDs, including the ibuprofen component of COMBOGESIC IV, has resulted in renal papillary necrosis and other renal injury. (5.7)
• Anaphylactic Reactions: Discontinue use immediately if symptoms occur. (5.8)
• Exacerbation of Asthma Related to Aspirin Sensitivity: COMBOGESIC IV is contraindicated in patients with aspirin-sensitive asthma. Monitor patients with preexisting asthma (without aspirin sensitivity). (5.9)
• Serious Skin Reactions: Discontinue COMBOGESIC IV at first appearance of skin rash or other signs of hypersensitivity. (5.10)
• Drug Rash with Eosinophilia and Systemic Symptoms (DRESS): Discontinue and evaluate clinically. (5.11)
• Fetal Toxicity: Limit use of NSAID-containing products, including COMBOGESIC IV, between about 20 to 30 weeks in pregnancy due to the risk of oligohydramnios/fetal renal dysfunction. Avoid use of NSAID-containing products, including COMBOGESIC IV, in women at about 30 weeks gestation and later in pregnancy due to the risks of oligohydramnios/fetal renal dysfunction and premature closure of the fetal ductus arteriosus. (5.12)
• Hematologic Toxicity: Monitor hemoglobin or hematocrit in patients with any signs or symptoms of anemia (5.13).

6 ADVERSE REACTIONS

The most common adverse reactions (greater than or equal to 3%) are infusion site pain, nausea, constipation, dizziness, infusion site extravasation, vomiting, headache, somnolence. (6.1)
To report SUSPECTED ADVERSE REACTIONS, contact Hikma Pharmaceuticals USA Inc. at 1-877-845-0689 or FDA at 1-800-FDA-1088 or www.fda.gov/medwatch.

7 DRUG INTERACTIONS

A number of known or potential interactions between COMBOGESIC IV and other drugs/drug classes exist. Please refer to the Drug Interactions section (7) for further information.

8 USE IN SPECIFIC POPULATIONS

- COMBOGESIC IV is not recommended in patients with renal impairment. (5.7, 8.7)
- COMBOGESIC IV is not recommended in patients with hepatic impairment. (5.2, 8.6)

See 17 for PATIENT COUNSELING INFORMATION

FULL PRESCRIBING INFORMATION

BOXED WARNING

WARNING: HEPATOTOXICITY, CARDIOVASCULAR RISK, and GASTROINTESTINAL RISK

RISK OF MEDICATION ERRORS: Take care when prescribing, preparing, and administering COMBOGESIC IV to avoid dosing errors which could result in accidental overdose and death (5.1).

HEPATOTOXICITY: COMBOGESIC IV contains acetaminophen. Acetaminophen has been associated with cases of acute liver failure, at times resulting in liver transplant and death. Most of the cases of liver injury are associated with doses of acetaminophen that exceed 4,000 mg per day, and often involve more than one acetaminophen-containing product [see Warnings and Precautions (5.2)].

CARDIOVASCULAR RISK: COMBOGESIC IV contains ibuprofen, a nonsteroidal anti-inflammatory drug (NSAID). NSAIDs cause an increased risk of serious cardiovascular thrombotic events, including myocardial infarction and stroke, which can be fatal. This risk may occur early in treatment and may
increase with duration of use [see Warnings and Precautions (5.3)].

COMBOGESIC IV is contraindicated for treatment of peri-operative pain in the setting of coronary artery bypass graft (CABG) surgery [see Contraindications (4) and Warnings and Precautions (5.3)].

GASTROINTESTINAL RISK: NSAIDs cause an increased risk of serious gastrointestinal adverse events including bleeding, ulceration, and perforation of the stomach or intestines, which can be fatal. These events can occur at any time during use and without warning symptoms. Elderly patients are at greater risk for serious gastrointestinal events [see Warnings and Precautions (5.4)].

1 INDICATIONS AND USAGE

COMBOGESIC IV is indicated in adults where an intravenous route of administration is considered clinically necessary for:
• the relief of mild to moderate pain
• the management of moderate to severe pain as an adjunct to opioid analgesics
Limitations of Use
COMBOGESIC IV is indicated for short-term use of five days or less.

2 DOSAGE AND ADMINISTRATION

2.1 Important Dosage and Administration Instructions

• Use the lowest effective dosage for the shortest duration consistent with individual patient treatment goals [see Warnings and Precautions (5.4)].
• Do not exceed the maximum total daily dose of COMBOGESIC IV (4,000 mg acetaminophen and 1,200 mg ibuprofen) in 24 hours.
• Do not exceed a total daily dose of 4,000 mg (4 g) acetaminophen from all sources.
• Do not co-administer COMBOGESIC IV with other acetaminophen or ibuprofen containing products [see Warnings and Precautions (5.2)].
• Visually inspect for particulate matter and discoloration prior to administration. If visibly opaque particles, discoloration, or other foreign particulates are observed, do not use.
• Use COMBOGESIC IV in one patient on one occasion only. It contains no antimicrobial preservative. Discard any unused solution.
• Do not mix with diluents or with other medicines.

2.2 Recommended Dosage

For adult patients weighing greater than or equal to 50 kg (actual body weight): The recommended dosage of COMBOGESIC IV is one vial (100 mL; acetaminophen 1,000 mg/ibuprofen 300 mg) administered as a 15-minute infusion every 6 hours, as necessary.

For adult patients weighing less than 50 kg (actual body weight): The recommended dosage is 15 mg/kg acetaminophen and 4.5 mg/kg ibuprofen, administered as a 15-minute infusion every 6 hours, as necessary. This equates to a maximum single dose of 750 mg acetaminophen and 225 mg ibuprofen (discard remaining medicine in vial), and a total daily dose of 3,000 mg (3 g) acetaminophen and 900 mg ibuprofen.

2.3 Instructions for Intravenous Administration

• Administer as a 15-minute intravenous infusion.
• Do not mix other medications with the COMBOGESIC IV vial or infusion device.
• As for all solutions for infusion presented in glass vials, monitor closely, particularly at the end of infusion, regardless of administration route, in order to avoid air embolism. This applies particularly for central route infusion.
• To decrease the likelihood of bung fragmentation or the bung being forced into the vial, use a syringe or giving set with a diameter equal to or below 0.8 mm for solution sampling and ensure that the bung is pierced at the location specifically designed for needle introduction (where the thickness of the bung is the lowest).
• The entire 100 mL container of COMBOGESIC IV is not intended for use in patients weighing less than 50 kg. For doses less than 1,000 mg acetaminophen and 300 mg ibuprofen, the appropriate dose must be withdrawn from the container and placed into a separate container prior to administration. Using aseptic technique, withdraw the appropriate dose (weight-based) from an intact sealed COMBOGESIC IV container and place the measured dose in a separate empty, sterile container (e.g., glass bottle, plastic intravenous container, or syringe) for intravenous infusion to avoid the inadvertent delivery and administration of the total volume of the commercially available container. COMBOGESIC IV is supplied in a single-dose container and the unused portion must be discarded.

3 DOSAGE FORMS AND STRENGTHS

Injection: 1,000 mg/100 mL (10 mg/mL) of acetaminophen and 300 mg/100 mL (3 mg/mL) of ibuprofen in a clear, colorless solution in single-dose vial.

4 CONTRAINDICATIONS

COMBOGESIC IV is contraindicated in:
• patients with a known hypersensitivity (e.g., anaphylactic reactions and serious skin reactions) to acetaminophen, ibuprofen, other NSAIDs or to any other components of this product [see Warnings and Precautions (5.8, 5.10, 5.11)]
• patients with a history of asthma, urticaria, or other allergic-type reactions after taking aspirin or other NSAIDs. Severe, sometimes fatal, anaphylactic reactions to NSAIDs have been reported in such patients [see Warnings and Precautions (5.8, 5.9)]
• in the setting of coronary artery bypass graft (CABG) surgery [see Warnings and Precautions (5.3)]
• patients with severe hepatic impairment or severe active liver disease [see Warnings and Precautions (5.2)]

5 WARNINGS AND PRECAUTIONS

5.1 Risk of Medication Errors

Take care when prescribing, preparing, and administering COMBOGESIC IV in order to avoid dosing errors which could result in accidental overdose and death. In particular, be careful to ensure that:
• the dose in milligrams (mg) and milliliters (mL) is not confused;
• the dosing is based on weight for patients under 50 kg;
• infusion pumps are properly programmed; and
• the total daily dose of acetaminophen from all sources does not exceed maximum daily limits [see Dosage and Administration (2)].

5.2 Hepatotoxicity

Acetaminophen
COMBOGESIC IV contains acetaminophen. Acetaminophen has been associated with cases of acute liver failure, at times resulting in liver transplant and death. Most of the cases of liver injury are associated with the use of acetaminophen at doses that exceed 4,000 mg per day, and often involve more than one acetaminophen-containing product.

The risk of acute liver failure is higher in individuals with underlying liver disease and in individuals who ingest alcohol while taking acetaminophen.

Ibuprofen
COMBOGESIC IV contains ibuprofen, a NSAID. Elevations of ALT or AST (three or more times the upper limit of normal [ULN]) have been reported in approximately 1% of NSAID-treated patients in clinical trials. In addition, rare, sometimes fatal, cases of severe hepatic injury, including fulminant hepatitis, liver necrosis, and hepatic failure have been reported.

Elevations of ALT or AST (less than three times ULN) may occur in up to 15% of patients treated with NSAIDs, including ibuprofen.

Clinical Recommendations
COMBOGESIC IV is contraindicated in patients with severe hepatic impairment or severe active liver disease. COMBOGESIC IV has not been studied in patients with impaired hepatic function. Use in these patients is not recommended [see Use in Specific Populations (8.6)].

If clinical signs and symptoms consistent with liver disease develop, or if systemic manifestations occur (e.g., eosinophilia, rash, etc.), discontinue COMBOGESIC IV immediately, and perform a clinical evaluation of the patient.

5.3 Cardiovascular Thrombotic Events

Clinical trials of several COX-2 selective and nonselective NSAIDs of up to three years duration have shown an increased risk of serious cardiovascular (CV) thrombotic events, including myocardial infarction (MI) and stroke, which can be fatal. Based on available data, it is unclear that the risk for CV thrombotic events is similar for all NSAIDs. The relative increase in serious CV thrombotic events over baseline conferred by NSAID use appears to be similar in those with and without known CV disease or risk factors for CV disease. However, patients with known CV disease or risk factors had a higher absolute incidence of excess serious CV thrombotic events, due to their increased baseline rate. Some observational studies found that this increased risk of serious CV thrombotic events began as early as the first weeks of treatment. The increase in CV thrombotic risk has been observed most consistently at higher doses.

To minimize the potential risk for an adverse CV event in NSAID-treated patients, the lowest effective dose for the shortest duration possible should be used. Physicians and patients should remain alert for the development of such events, throughout the entire treatment course, even in the absence of previous CV symptoms. Patients should be informed about the symptoms of serious CV events and the steps to take if they occur.

There is no consistent evidence that concurrent use of aspirin mitigates the increased risk of serious CV thrombotic events associated with NSAID use. The concurrent use of aspirin and an NSAID, such as ibuprofen, increases the risk of serious gastrointestinal (GI) events [see Warnings and Precautions (5.4)].

Status Post Coronary Artery Bypass Graft (CABG) Surgery
Two large, controlled clinical trials of a COX-2 selective NSAID for the treatment of pain in the first 10-14 days following CABG surgery found an increased incidence of myocardial infarction and stroke. NSAIDs are contraindicated in the setting of CABG [see Contraindications (4)].

Post-MI Patients
Observational studies conducted in the Danish National Registry have demonstrated that patients treated with NSAIDs in the post-MI period were at increased risk of reinfarction, CV-related death, and all-cause mortality beginning in the first week of treatment. In this same cohort, the incidence of death in the first year post-MI was 20 per 100 person years in NSAID-treated patients compared to 12 per 100 person years in non-NSAID exposed patients. Although the absolute rate of death declined somewhat after the first year post-MI, the increased relative risk of death in NSAID users persisted over at least the next four years of follow-up.

Avoid the use of COMBOGESIC IV in patients with a recent MI unless the benefits are expected to outweigh the risk of recurrent CV thrombotic events. If COMBOGESIC IV is used in patients with a recent MI, monitor patients for signs of cardiac ischemia.

5.4 Gastrointestinal Bleeding, Ulceration, and Perforation

NSAIDs, including ibuprofen, cause serious gastrointestinal (GI) adverse events including inflammation, bleeding, ulceration, and perforation of the esophagus, stomach, small intestine, or large intestine, which can be fatal. These serious adverse events can occur at any time, with or without warning symptoms, in patients treated with NSAIDs. Only one in five patients who develop a serious upper GI adverse event on NSAID therapy is symptomatic. Upper GI ulcers, gross bleeding, or perforation caused by NSAIDs occurred in approximately 1% of patients treated for 3-6 months and in about 2-4% of patients treated for one year. However, even short-term therapy is not without risk.

Risk Factors for GI Bleeding, Ulceration and Perforation
Patients with a prior history of peptic ulcer disease and/or GI bleeding who used NSAIDs had a greater than 10-fold increased risk for developing a GI bleed compared to patients without these risk factors. Other factors that increase the risk of GI bleeding in patients treated with NSAIDs include longer duration of NSAID therapy; concomitant use of oral corticosteroids, aspirin, anticoagulants, or selective serotonin reuptake inhibitors (SSRIs); smoking; use of alcohol; older age; and poor general health status. Most post-marketing reports of fatal GI events occurred in elderly or debilitated patients. Additionally, patients with advanced liver disease and/or coagulopathy are at increased risk for getting an ulcer or bleeding.

Strategies to Minimize the GI Risks in NSAID-treated Patients
• Use the lowest effective dosage for the shortest possible duration.
• Avoid administration of more than one NSAID at a time.
• Avoid use in patients at higher risk, unless benefits are expected to outweigh the increased risk of bleeding. For such patients, as well as those with active GI bleeding, consider alternate therapies other than NSAIDs.
• Remain alert for signs and symptoms of GI ulceration and bleeding during NSAID therapy.
• If a serious GI adverse event is suspected, promptly initiate evaluation and treatment, and discontinue COMBOGESIC IV until a serious GI adverse event is ruled out.
• In the setting of concomitant use of low-dose aspirin for cardiac prophylaxis, monitor patients more closely for evidence of GI bleeding [see Drug Interactions (7)].

5.5 Hypertension

NSAIDs, including the ibuprofen in COMBOGESIC IV, can lead to onset of new hypertension or worsening of preexisting hypertension, either of which may contribute to the increased incidence of CV events. Patients taking angiotensin converting enzyme (ACE) inhibitors, thiazide diuretics, or loop diuretics may have impaired response to these therapies when taking NSAIDs. Monitor blood pressure (BP) during the initiation of NSAID treatment and throughout the course of therapy.

5.6 Heart Failure and Edema

The Coxib and traditional NSAID Trialists’ Collaboration meta-analysis of randomized controlled trials demonstrated an approximately two-fold increase in hospitalizations for heart failure in COX-2 selective-treated patients and nonselective NSAID-treated patients compared to placebo-treated patients. In a Danish National Registry study of patients with heart failure, NSAID use increased the risk of MI, hospitalization for heart failure, and death.

Additionally, fluid retention and edema have been observed in some patients treated with NSAIDs. Use of ibuprofen may blunt the CV effects of several therapeutic agents used to treat these medical conditions (e.g., diuretics, ACE inhibitors, or angiotensin receptor blockers [ARBs]) [see Drug Interactions (7)].

Avoid the use of COMBOGESIC IV in patients with severe heart failure unless the benefits are expected to outweigh the risk of worsening heart failure. If COMBOGESIC IV is used in patients with severe heart failure, monitor patients for signs of worsening heart failure.

5.7 Renal Toxicity and Hyperkalemia

Renal Toxicity
Use of COMBOGESIC IV is not recommended in patients with renal impairment.

Long-term administration of NSAIDs, including the ibuprofen component of COMBOGESIC IV, has resulted in renal papillary necrosis and other renal injury.

Renal toxicity has also been seen in patients in whom renal prostaglandins have a compensatory role in the maintenance of renal perfusion. In these patients, administration of a NSAID may cause a dose-dependent reduction in prostaglandin formation and, secondarily, in renal blood flow, which may precipitate overt renal decompensation. Patients at greatest risk of this reaction are those with impaired renal function, dehydration, hypovolemia, heart failure, liver dysfunction, those taking diuretics and ACE inhibitors or ARBs, and the elderly. Discontinuation of NSAID therapy is usually followed by recovery to the pretreatment state.

No information is available from controlled clinical studies regarding the use of COMBOGESIC IV in patients with advanced renal disease. The renal effects of COMBOGESIC IV may hasten the progression of renal dysfunction in patients with pre-existing renal disease.

Correct volume status in dehydrated or hypovolemic patients prior to initiating COMBOGESIC IV.

Hyperkalemia
Increases in serum potassium concentration, including hyperkalemia, have been reported with use of NSAIDs,even in some patients without renal impairment. In patients with normal renal function, these effects have been attributed to a hyporeninemic-hypoaldosteronism state.

5.8 Hypersensitivity and Anaphylactic Reactions

Acetaminophen
There have been post-marketing reports of hypersensitivity and anaphylaxis associated with the use of acetaminophen. Clinical signs included swelling of the face, mouth, and throat, respiratory distress, urticaria, rash, pruritus, and vomiting. There were infrequent reports of life-threatening anaphylaxis requiring emergency medical attention. Discontinue COMBOGESIC IV immediately if symptoms associated with allergy or hypersensitivity occur. Do not use COMBOGESIC IV in patients with acetaminophen allergy.

Ibuprofen
NSAIDS, including the ibuprofen in COMBOGESIC IV, has been associated with anaphylactic reactions in patients with and without known hypersensitivity to ibuprofen and in patients with aspirin-sensitive asthma [see Contraindications (4) and Warnings and Precautions (5.9)]. Discontinue COMBOGESIC IV immediately if symptoms associated with allergy or hypersensitivity occur.

5.9 Exacerbation of Asthma Related to Aspirin Sensitivity

A subpopulation of patients with asthma may have aspirin-sensitive asthma which may include chronic rhinosinusitis complicated by nasal polyps; severe, potentially fatal bronchospasm; and/or intolerance to aspirin and other NSAIDs. Because cross-reactivity between aspirin and other NSAIDs has been reported in such aspirin-sensitive patients, COMBOGESIC IV is contraindicated in patients with this form of aspirin sensitivity [see Contraindications (4)]. When COMBOGESIC IV is used in patients with preexisting asthma
(without known aspirin sensitivity), monitor patients for changes in the signs and symptoms of asthma.

5.10 Serious Skin Reactions

COMBOGESIC IV contains acetaminophen and ibuprofen. Acetaminophen, or NSAIDs, including ibuprofen, may cause serious skin reactions such as exfoliative dermatitis, acute generalized exanthematous pustulosis (AGEP), Stevens-Johnson Syndrome (SJS), and toxic epidermal necrolysis (TEN), which can be fatal. NSAIDs can also cause fixed drug eruption (FDE). FDE may present as a more severe variant known as generalized bullous fixed drug eruption (GBFDE), which can be life-threatening. These serious events may occur without warning. Inform patients about the signs and symptoms of serious skin reactions, and discontinued the use of the drug at the first appearance of skin rash or any other
sign of hypersensitivity. COMBOGESIC IV is contraindicated in patients with previous serious skin reactions to acetaminophen or NSAIDs [see Contraindications (4)].

5.11 Drug Rash with Eosinophilia and Systemic Symptoms (DRESS)

Drug Reaction with Eosinophilia and Systemic Symptoms (DRESS) has been reported in patients taking NSAIDs such as the ibuprofen in COMBOGESIC IV. Some of these events have been fatal or life-threatening. DRESS typically, although not exclusively, presents with fever, rash, lymphadenopathy, and/or facial swelling. Other clinical manifestations may include hepatitis, nephritis, hematological abnormalities, myocarditis, or myositis. Sometimes symptoms of DRESS may resemble an acute viral infection. Eosinophilia is often present. Because this disorder is variable in its presentation, other organ systems not noted here may be involved. It is important to note that early manifestations of hypersensitivity, such as fever or lymphadenopathy, may be present even though rash is not evident. If such signs or symptoms are present, discontinue COMBOGESIC
IV and evaluate the patient immediately.

5.12 Fetal Toxicity

Premature Closure of Fetal Ductus Arteriosus
Avoid use of NSAID-containing products, including COMBOGESIC IV, in pregnant women at about 30 weeks gestation and later. NSAID-containing products, including COMBOGESIC IV, increase the risk of premature closure of the fetal ductus arteriosus at approximately this gestational age.

Oligohydramnios/Neonatal Renal Impairment
Use of NSAID-containing products, including COMBOGESIC IV, at about 20 weeks gestation or later in pregnancy may cause fetal renal dysfunction leading to oligohydramnios and, in some cases, neonatal renal impairment. These adverse outcomes are seen, on average, after days to weeks of treatment, although oligohydramnios has been infrequently reported as soon as 48 hours after NSAID initiation. Oligohydramnios is often, but not always, reversible with treatment discontinuation. Complications of prolonged oligohydramnios may, for example, include limb contractures and delayed lung maturation. In some post-marketing cases of impaired neonatal renal function, invasive procedures such as exchange transfusion or dialysis were required.

If, after careful consideration of alternative treatment options for pain management, NSAID treatment is necessary between about 20 weeks and 30 weeks gestation, limit COMBOGESIC IV use to the lowest effective dose and shortest duration possible. Consider ultrasound monitoring of amniotic fluid if COMBOGESIC IV treatment extends beyond 48 hours. Discontinue COMBOGESIC IV if oligohydramnios occurs and follow up according to clinical practice [see Use in Specific Populations (8.1)].

5.13 Hematologic Toxicity

Anemia has occurred in NSAID-treated patients. This may be due to occult or gross GI blood loss, fluid retention, or an incompletely described effect on erythropoiesis. If a patient being treated with COMBOGESIC IV has any signs or symptoms of anemia, monitor hemoglobin or hematocrit.

NSAIDs, including the ibuprofen in COMBOGESIC IV, may increase the risk of bleeding events. Co-morbid conditions such as coagulation disorders or concomitant use of warfarin, other anticoagulants, antiplatelet agents (e.g., aspirin), serotonin reuptake inhibitors (SSRIs) and serotonin norepinephrine reuptake inhibitors (SNRIs) may increase this risk. Monitor these patients for signs of bleeding [see Drug Interactions (7)].

5.14 Ophthalmological Effects

Blurred or diminished vision, scotomata, and/or changes in color vision have been reported with oral ibuprofen. If a patient develops such complaints while receiving COMBOGESIC IV, the drug should be discontinued, and the patient should have an ophthalmologic examination which includes central visual fields and color vision testing.

5.15 Aseptic Meningitis

Aseptic meningitis with fever and coma has been observed in patients on oral ibuprofen. Although it is probably more likely to occur in patients with systemic lupus erythematosus and related connective tissue diseases, it has been reported in patients who do not have underlying chronic disease. If signs or symptoms of meningitis develop in a patient on COMBOGESIC IV, the possibility of its being related to ibuprofen should be considered.

5.16 Masking of Inflammation and Fever

The pharmacological activity of COMBOGESIC IV in reducing inflammation, and possibly fever, may diminish the utility of diagnostic signs in detecting infections.

5.17 Laboratory Monitoring

Because serious GI bleeding, hepatotoxicity, and renal injury can occur without warning symptoms or signs, consider monitoring patients on NSAID treatment with a CBC and a chemistry profile as clinically indicated [see Warnings and Precautions (5.3,5.4,5.8)].

6 ADVERSE REACTIONS

The following clinically significant adverse reactions to ibuprofen or acetaminophen are described elsewhere in other sections of the labelling.
• Hepatotoxicity [see Warnings and Precautions (5.2)]
• Cardiovascular Thrombotic Events [see Warnings and Precautions (5.3)]
• Gastrointestinal Bleeding, Ulceration, and Perforation [see Warnings and Precautions (5.4)]
• Hypertension [see Warnings and Precautions (5.5)]
• Heart Failure and Edema [see Warnings and Precautions (5.6)]
• Renal Toxicity and Hyperkalemia [see Warnings and Precautions (5.7)]
• Hypersensitivity and Anaphylactic Reactions [see Warnings and Precautions (5.8)]
• Exacerbation of Asthma Related to Aspirin Sensitivity [see Warnings and Precautions (5.9)]
• Serious Skin Reactions [see Warnings and Precautions (5.10)]
• Drug Rash with Eosinophilia and Systemic Symptoms (DRESS) [see Warnings and Precautions (5.11)]
• Hematologic Toxicity [see Warnings and Precautions (5.13)]

6.1 Clinical Trials Experience

Because clinical trials are conducted under widely varying conditions, adverse reaction rates observed in the clinical trials of a drug cannot be directly compared to rates in the clinical trials of another drug and may not reflect the rates observed in practice.

The clinical trials of COMBOGESIC IV have been conducted in patients with postoperative musculoskeletal pain and soft tissue pain models lasting between two to five days. Two Phase 3 clinical trials have been conducted with COMBOGESIC IV to assess efficacy and safety after multiple doses. In AFT-MXIV-07 participants were treated with COMBOGESIC IV, acetaminophen IV, ibuprofen IV or placebo for a treatment period of 48 hours. In AFT-MXIV-11 participants were treated for between 48 hours and five days with COMBOGESIC IV. The study population for AFT-MXIV-07 was comprised of adults aged 18 to 65 years, mean age: 42 years. AFT-MXIV-11 included adults aged 19 – 87 years, mean age: 53 years.

Safety data for the first 48 hours of both studies was pooled. Overall, 59.3% of the patients (N = 182/307) administered COMBOGESIC IV experienced one or more treatment-emergent adverse event (TEAE) during the first 48 hours of treatment, accounting for a total of 436 TEAEs (see Table 1). The most common TEAEs were related to the infusion site (infusion site pain, infusion site extravasation), or affected the gastrointestinal (nausea, vomiting, constipation) or nervous (dizziness, headache, somnolence) systems.

Table 1: Common TEAEs (occurring in ≥ 3% of COMBOGESIC IV-treated participants)

Adverse Reactions | COMBOGESIC IV (N=307) % | Acetaminophen (N=75) % | Ibuprofen (N=76) % | Placebo (N=50) %
Gastrointestinal disorders
Nausea | 16.3 | 33.3 | 34.2 | 32.0
Vomiting | 6.2 | 14.7 | 6.6 | 2.0
Constipation | 7.2 | 5.3 | 5.3 | 8.0
Infusion Site Complications
Infusion site pain | 17.6 | 0.0 | 9.2 | 2.0
Infusion site extravasation | 6.5 | 2.7 | 6.6 | 14.0
Nervous System Disorders
Headache | 5.5 | 6.7 | 6.6 | 20.0
Dizziness | 7.2 | 9.3 | 9.2 | 18.0
Somnolence | 3.9 | 8.0 | 7.9 | 6.0

Other skin and subcutaneous-related TEAEs (pruritis, hyperhidrosis) also affected around 2-3% of the study population, as did procedural nausea and polyuria.

AFT-MXIV-11 found no notable difference in the safety profile of COMBOGESIC IV in participants treated for 5 days compared to those treated for 48 hours. Additionally, the safety profile was comparable between older participants (aged 65-75 years and >75 years) and younger participants (aged <65 years); the type and incidence of treatment-emergent adverse events was comparable, and the incidence of clinically significant shifts in laboratory tests (hematocrit 1.3% (n=3/228), hemoglobin 1.3% (n=3/228) and erythrocytes 0.9% (n=2/218), was low in participants over the age of 65.

6.2 Postmarketing Experience

The following adverse reactions have been identified during postapproval use of acetaminophen and ibuprofen. Because these reactions are reported voluntarily from a population of uncertain size, it is not always possible to reliably estimate their frequency or establish a causal relationship to drug exposure.

Skin and Appendages: Exfoliative dermatitis, Stevens-Johnson Syndrome (SJS), toxic epidermal necrolysis (TEN), and fixed drug eruption (FDE).

7 DRUG INTERACTIONS

Table 2. Drug Interactions with COMBOGESIC IV

Drugs That Interfere with Hemostasis
Clinical Impact: | • Ibuprofen and anticoagulants such as warfarin have a synergistic effect on bleeding. The concomitant use of ibuprofen and anticoagulants have an increased risk of serious bleeding compared to the use of either drug alone. • Serotonin release by platelets plays an important role in hemostasis. Case-control and cohort epidemiological studies showed that concomitant use of drugs that interfere with serotonin reuptake and an NSAID may potentiate the risk of bleeding more than an NSAID alone.
Intervention: | Monitor patients with concomitant use of COMBOGESIC IV with anticoagulants (e.g., warfarin), antiplatelet agents (e.g., aspirin), selective serotonin reuptake inhibitors (SSRIs), and serotonin norepinephrine reuptake inhibitors (SNRIs) for signs of bleeding [see Warnings and Precautions (5.13)].
Aspirin
Clinical Impact: | Controlled clinical studies showed that the concomitant use of NSAIDs and analgesic doses of aspirin does not produce any greater therapeutic effect than the use of NSAIDs alone. In a clinical study, the concomitant use of an NSAID and aspirin was associated with a significantly increased incidence of GI adverse reactions as compared to use of the NSAID alone [see Warnings and Precautions (5.3)].
Intervention: | Concomitant use of COMBOGESIC IV and analgesic doses of aspirin is not generally recommended because of the increased risk of bleeding [see Warnings and Precautions (5.4, 5.13)]. COMBOGESIC IV is not a substitute for low dose aspirin for cardiovascular protection.
ACE Inhibitors, Angiotensin Receptor Blockers, and Beta-Blockers
Clinical Impact: | • NSAIDs may diminish the antihypertensive effect of angiotensin converting enzyme (ACE) inhibitors, angiotensin receptor blockers (ARBs), or beta-blockers (including propranolol). • In patients who are elderly, volume-depleted (including those on diuretic therapy), or have renal impairment, co-administration of an NSAID with ACE inhibitors or ARBs may result in deterioration of renal function, including possible acute renal failure. These effects are usually reversible.
Intervention: | • During concomitant use of COMBOGESIC IV and ACE-inhibitors, ARBs, or betablockers, monitor blood pressure to ensure that the desired blood pressure is obtained. • During concomitant use of COMBOGESIC IV and ACE-inhibitors or ARBs in patients who are elderly, volume-depleted, or have impaired renal function, monitor for signs of worsening renal function [see Warnings and Precautions (5.7)]. • When these drugs are administered concomitantly, patients should be adequately hydrated. Assess renal function at the beginning of the concomitant treatment and periodically thereafter.
Diuretics
Clinical Impact: | Clinical studies, as well as post-marketing observations, showed that NSAIDs reduced the natriuretic effect of loop diuretics (e.g., furosemide) and thiazide diuretics in some patients. This effect has been attributed to the NSAID inhibition of renal prostaglandin synthesis.
Intervention: | During concomitant use of COMBOGESIC IV with diuretics, observe patients for signs of worsening renal function, in addition to assuring diuretic efficacy including antihypertensive effects [see Warnings and Precautions (5.7)].
Digoxin
Clinical Impact: | The concomitant use of ibuprofen with digoxin has been reported to increase the serum concentration and prolong the half-life of digoxin.
Intervention: | During concomitant use of COMBOGESIC IV and digoxin, monitor serum digoxin levels.
Lithium
Clinical Impact: | NSAIDs have produced elevations in plasma lithium levels and reductions in renal lithium clearance. The mean minimum lithium concentration increased 15%, and the renal clearance decreased by approximately 20%. This effect has been attributed to NSAID inhibition of renal prostaglandin synthesis.
Intervention: | During concomitant use of COMBOGESIC IV and lithium, monitor patients for signs of lithium toxicity.
Methotrexate
Clinical Impact: | Concomitant use of NSAIDs and methotrexate may increase the risk for methotrexate toxicity (e.g., neutropenia, thrombocytopenia, renal dysfunction).
Intervention: | During concomitant use of COMBOGESIC IV and methotrexate, monitor patients for methotrexate toxicity.
Cyclosporine
Clinical Impact: | Concomitant use of NSAIDS and cyclosporine may increase cyclosporine’s nephrotoxicity.
Intervention: | During concomitant use of COMBOGESIC IV and cyclosporine, monitor patients for signs of worsening renal function.
NSAIDs and Salicylates
Clinical Impact: | Concomitant use of ibuprofen with other NSAIDs or salicylates (e.g., diflunisal, salsalate) increases the risk of GI toxicity, with little or no increase in efficacy [see Warnings and Precautions (5.4)].
Intervention: | The concomitant use of ibuprofen with other NSAIDs or salicylates is not recommended.
Pemetrexed
Clinical Impact: | Concomitant use of NSAIDS and pemetrexed may increase the risk of pemetrexed-associated myelosuppression, renal, and GI toxicity (see the pemetrexed prescribing information).
Intervention: | During concomitant use of COMBOGESIC IV and pemetrexed, in patients with renal impairment whose creatinine clearance ranges from 45 to 79 mL/min, monitor for myelosuppression, renal and GI toxicity. NSAIDs with short elimination half-lives (e.g., diclofenac, indomethacin) should be avoided for a period of two days before, the day of, and two days following administration of pemetrexed. In the absence of data regarding potential interaction between pemetrexed and NSAIDs with longer half-lives (e.g., meloxicam, nabumetone), patients taking these NSAIDs should interrupt dosing for at least five days before, the day of, and two days following pemetrexed administration.

8 USE IN SPECIFIC POPULATIONS

8.1 Pregnancy

Risk Summary

Use of NSAID-containing products, including COMBOGESIC IV, can cause premature closure of the fetal ductus arteriosus and fetal renal dysfunction leading to oligohydramnios and, in some cases, neonatal renal impairment. Because of these risks, limit dose and duration of COMBOGESIC IV use between about 20 and 30 weeks of gestation and avoid COMBOGESIC IV use at about 30 weeks of gestation and later in pregnancy (see Clinical Considerations, Data).

Premature Closure of Fetal Ductus Arteriosus:

Use of NSAID-containing products, including COMBOGESIC IV, at about 30 weeks gestation or later in pregnancy increases the risk of premature closure of the fetal ductus arteriosus.

Oligohydramnios/Neonatal Renal Impairment:

Use of NSAID-containing products, including COMBOGESIC IV, at about 20 weeks gestation or later in pregnancy has been associated with cases of fetal renal dysfunction leading to oligohydramnios, and in some cases, neonatal renal impairment.

Data from observational studies regarding other potential embryofetal risks of NSAID use in women in the first or second trimester of pregnancy are inconclusive.

No adequate and well-controlled studies have been conducted using COMBOGESIC IV in pregnant women. Animal reproduction studies have also not been conducted with COMBOGESIC IV.

The following describes animal reproduction studies for Acetaminophen and Ibuprofen:

Acetaminophen: Reproductive and developmental studies in rats and mice from the published literature have identified adverse events at clinically relevant doses of acetaminophen. Fetotoxicity, increases in bone variations in the fetuses, and necrosis in the fetus liver and kidney have been noted in studies in rats. In mice treated with acetaminophen at doses within the clinical dosing range, cumulative adverse effects on reproduction were seen in a continuous breeding study. A reduction in number of litters of the parental mating pair was observed as well as retarded growth and abnormal sperm in their offspring and reduced birth weight in the next generation (see Data).

Ibuprofen: Reproductive studies conducted in rats and rabbits have not demonstrated evidence of developmental abnormalities after ibuprofen exposure. However, animal reproduction studies are not always predictive of human response. There are no adequate and well-controlled studies in pregnant women and ibuprofen should be used in pregnancy only if the potential benefit justifies the potential risk to the fetus (see Data).

Based on animal data, prostaglandins have been shown to have an important role in endometrial vascular permeability, blastocyst implantation, and decidualization. In animal studies, administration of prostaglandin synthesis inhibitors such as ibuprofen, resulted in increased pre- and post-implantation loss. Prostaglandins also have been shown to have an important role in fetal kidney development. In published animal studies, prostaglandin synthesis inhibitors have been reported to impair kidney development when administered at clinically relevant doses (see Data).

The estimated background risk of major birth defects and miscarriages for the indicated population is unknown. All pregnancies have a background risk of birth defect, loss, or other adverse outcomes. In the general U.S. population, the estimated background risk of major birth defects and miscarriage in clinically recognized pregnancies is 2-4% and 15-20%, respectively.

Clinical Considerations

Fetal/Neonatal Adverse Reactions

Premature Closure of Fetal Ductus Arteriosus:

Avoid use of NSAID-containing products, including COMBOGESIC IV, in women at about 30 weeks gestation and later in pregnancy, because NSAIDs, including COMBOGESIC IV, can cause premature closure of the fetal ductus arteriosus (see Data).

Oligohydramnios/Neonatal Renal Impairment:

If, after consideration of alternative treatments for pain management, an NSAID-containing product, including COMBOGESIC IV, is necessary at about 20 weeks gestation or later in pregnancy, limit the use to the lowest effective dose and shortest duration possible. If COMBOGESIC IV treatment extends beyond 48 hours, consider monitoring with ultrasound for oligohydramnios. If oligohydramnios occurs, discontinue COMBOGESIC IV and follow up according to clinical practice (see Data).

Labor or Delivery

There are no studies on the effects of COMBOGESIC IV during labor or delivery.

In animal studies, NSAIDS, including ibuprofen, inhibit prostaglandin synthesis, cause delayed parturition, and increase the incidence of stillbirth.

Data

Human Data

Acetaminophen:

The results from a large population-based prospective cohort, including data from 26,424 women with live born singletons who were exposed to oral acetaminophen during the first trimester, indicate no increased risk for congenital malformations, compared to a control group of unexposed children. The rate of congenital malformations (4.3%) was similar to the rate in the general population. A population-based, case-control study from the National Birth Defects Prevention Study showed that 11,610 children with prenatal exposure to acetaminophen during the first trimester had no increased risk of major birth defects compared to 4,500 children in the control group. Other epidemiological data showed similar results. However, these studies cannot definitely establish the absence of any risk because of methodological limitations, including recall bias.

Ibuprofen:

Premature Closure of Fetal Ductus Arteriosus:

Published literature reports that the use of NSAIDs at about 30 weeks of gestation and later in pregnancy may cause premature closure of the fetal ductus arteriosus.

Oligohydramnios/Neonatal Renal Impairment:

Published studies and post-marketing reports describe maternal NSAID use at about 20 weeks gestation or later in pregnancy associated with fetal renal dysfunction leading to oligohydramnios, and in some cases, neonatal renal impairment. These adverse outcomes are seen, on average, after days to weeks of treatment, although oligohydramnios has been infrequently reported as soon as 48 hours after NSAID initiation. In many cases, but not all, the decrease in amniotic fluid was transient and reversible with cessation of the drug. There have been a limited number of case reports of maternal NSAID use and neonatal renal dysfunction without oligohydramnios, some of which were irreversible. Some cases of neonatal renal dysfunction required treatment with invasive procedures, such as exchange transfusion or dialysis.

Methodological limitations of these post-marketing studies and reports include lack of a control group; limited information regarding dose, duration, and timing of drug exposure; and concomitant use of other medications. These limitations preclude establishing a reliable estimate of the risk of adverse fetal and neonatal outcomes with maternal NSAID use. Because the published safety data on neonatal outcomes involved mostly preterm infants, the generalizability of certain reported risks to the full-term infant exposed to NSAIDs through maternal use is uncertain.

Animal Data

Acetaminophen:

Studies in pregnant rats that received oral acetaminophen during organogenesis at doses up to 0.85 times the maximum human daily dose (MHDD= 4 grams/day, based on a body surface area comparison) showed evidence of fetotoxicity (reduced fetal weight and length) and a dose-related increase in bone variations (reduced ossification and rudimentary rib changes). Offspring had no evidence of external, visceral, or skeletal malformations.

When pregnant rats received oral acetaminophen throughout gestation at doses of 1.2 times the MHDD (based on a body surface area comparison), areas of necrosis occurred in both the liver and kidney of pregnant rats and fetuses. These effects did not occur in animals that received oral acetaminophen at doses 0.3 times the MHDD (based on a body surface area comparison).

In a continuous breeding study, pregnant mice received 0.25, 0.5, or 1.0% acetaminophen via the diet (357, 715, or 1430 mg/kg/day). These doses are approximately 0.43, 0.87, and 1.7 times the MHDD, respectively, based on a body surface area comparison. A dose-related reduction in body weights of fourth and fifth litter offspring of the treated mating pair occurred during lactation and post-weaning at all doses. Animals in the high dose group had a reduced number of litters permating pair,male offspring with an increased percentage of abnormal sperm, and reduced birth weights in the next generation pups.

Ibuprofen:

In a published study, female rabbits given 7.5, 20, or 60 mg/kg ibuprofen (0.12, 0.32, or 0.97-times the maximum human daily dose of 1,200 mg of ibuprofen based on a body surface area comparison) from Gestation Days 1 to 29, no clear treatment-related adverse developmental effects were noted. This dose was associated with significant maternal toxicity (stomach ulcers, gastric lesions). In the same publication, female rats were administered 7.5, 20, 60, 180 mg/kg ibuprofen (0.06, 0.16, 0.48, 1.5-times the maximum daily dose) did not result in clear adverse developmental effects. Maternal toxicity (gastrointestinal lesions) was noted at 20 mg/kg and above.

In a published study, rats were orally dosed with 300 mg/kg ibuprofen (2.4-times the maximum human daily dose of 1,200 mg based on a body surface area comparison) during Gestation Days 9 and 10 (critical time points for heart development in rats). Ibuprofen treatment resulted in an increase in the incidence of membranous ventricular septal defects. This dose was associated with significant maternal toxicity including gastrointestinal toxicity. One incidence each of a membranous ventricular septal defect and gastroschisis was noted fetuses from rabbits treated with 500 mg/kg (8.1-times the maximum human daily dose) from Gestation Day 9 to 11.

8.2 Lactation

Risk Summary

The components of COMBOGESIC IV, ibuprofen and acetaminophen, are present in human milk. Limited published literature reports that, orally administered ibuprofen is present in human milk at relative infant doses of 0.06% to 0.6% of the maternal weight-adjusted daily dose. There are no reports of adverse effects of ibuprofen on the breastfed infant and no effects on milk production.

Limited published studies report that orally administered acetaminophen passes rapidly into human milk with similar levels in the milk and plasma. Average and maximum neonatal doses of 1% and 2%, respectively, of the weight-adjusted maternal dose are reported after a single oral administration of 1 gram acetaminophen. There is one well-documented report of a rash in a breast-fed infant that resolved when the mother stopped acetaminophen use and recurred when she resumed acetaminophen use.

The developmental and health benefits of breastfeeding should be considered along with the mother’s clinical need for COMBOGESIC IV and any potential adverse effects on the breastfed infant from COMBOGESIC IV or from the underlying maternal condition.

8.3 Females and Males of Reproductive Potential

Infertility

Acetaminophen

Based on animal data, use of acetaminophen may cause reduced fertility in males and females of reproductive potential. It is not known whether these effects on fertility are reversible.

Published studies in rodents report that oral acetaminophen treatment of male animals at doses that are approximately 1.2 times the MHDD and greater (based on a body surface area comparison) result in decreased testicular weights, reduced spermatogenesis, and reduced fertility. In female animals given the same doses, reduced implantation sites were reported. Additional published animal studies indicate that acetaminophen exposure in utero adversely impacts reproductive capacity of both male and female offspring at clinically relevant exposures [see Nonclinical Toxicology (13.1)].

Ibuprofen

Based on the mechanism of action, the use of prostaglandin-mediated NSAID-containing products, including COMBOGESIC IV, may delay or prevent rupture of ovarian follicles, which has been associated with reversible infertility in some women. Published animal studies have shown that administration of prostaglandin synthesis inhibitors has the potential to disrupt prostaglandin mediated follicular rupture required for ovulation. Small studies in women treated with NSAIDs have also shown a reversible delay in ovulation. Consider withdrawal of NSAID-containing products, including COMBOGESIC IV, in women who have difficulties conceiving or who are undergoing investigation of infertility.

8.4 Pediatric Use

The safety and effectiveness of COMBOGESIC IV in pediatric patients has not been studied in the pediatric population. COMBOGESIC IV is not approved for patients under 18 years of age.

8.5 Geriatric Use

Of the total number of subjects in clinical studies of COMBOGESIC IV, 20.2% (N = 62/307) were aged 65 years or over, including 5.2% (N = 16/307) aged 75 years or over [see Adverse Reactions (6.1)]. No overall differences in safety or effectiveness were observed between these subjects and younger subjects, and other reported clinical experience has not identified differences in responses between the elderly and younger patients, but greater sensitivity of some older individuals cannot be ruled out.

Elderly patients, compared to younger patients, are at greater risk for NSAID-associated serious cardiovascular, gastrointestinal, and/or renal adverse reactions. If the anticipated benefit for the elderly patient outweighs these potential risks, start dosing at the low end of the dosing range, and monitor patients for adverse effects [see Warnings and Precautions (5.2, 5.3, 5.4, 5.7)].

The ibuprofen and acetaminophen in COMBOGESIC IV are known to be substantially excreted by the kidney, and the risk of adverse reactions to this drug may be greater in patients with impaired renal function. Because elderly patients are more likely to have decreased renal function, care should be taken in dose selection, and it may be useful to monitor renal function.

8.6 Hepatic Impairment

COMBOGESIC IV has not been studied in patients with impaired hepatic function. Because acetaminophen is extensively metabolized by the liver, COMBOGESIC IV is contraindicated in patients with severe hepatic impairment or severe active liver disease. Use of COMBOGESIC IV in patients with hepatic impairment is not recommended [see Warnings and Precautions (5.2)].

8.7 Renal Impairment

COMBOGESIC IV has not been studied in patients with impaired renal function. The use of COMBOGESIC IV in these patients is not recommended [see Warnings and Precautions (5.7)].

10 OVERDOSAGE

COMBOGESIC IV is a combination product. The clinical presentation of overdose may include the signs and symptoms of acetaminophen toxicity, ibuprofen toxicity, or both.

Acetaminophen

The initial symptoms seen within the first 24 hours following an acetaminophen overdose are: anorexia, nausea, vomiting, malaise, pallor and diaphoresis.

In acute acetaminophen overdosage, dose-dependent, potentially fatal hepatic necrosis is the most serious adverse effect. Renal tubular necrosis, hypoglycemic coma, and thrombocytopenia also occur. Plasma acetaminophen levels > 300 mcg/mL at 4 hours after oral ingestion were associated with hepatic damage in 90% of patients; minimal hepatic damage is anticipated if plasma levels at 4 hours are < 150 mcg/mL or < 37.5 mcg/mL at 12 hours after ingestion [see Warnings and Precautions (5.2)].

Early symptoms following a potentially hepatotoxic overdose may include: nausea, vomiting, diaphoresis, and general malaise. Clinical and laboratory evidence of hepatic toxicity may not be apparent until 48 to 72 hours post-ingestion.

If an acetaminophen overdose is suspected, obtain a serum acetaminophen assay as soon as possible, but no sooner than 4 hours following oral ingestion. Obtain liver function studies initially and repeat at 24-hour intervals. Administer the antidote N-acetylcysteine (NAC) as early as possible. As a guide to treatment of acute ingestion, the acetaminophen level can be plotted against time since oral ingestion on a nomogram (Rumack- Matthew). The lower toxic line on the nomogram is equivalent to 150 mcg/mL at 4 hours and 37.5 mcg/mL at 12 hours. If serum level is above the lower line, administer the entire course of NAC treatment. Withhold NAC therapy if the acetaminophen level is below the lower line.

Ibuprofen

Symptoms following acute NSAID overdosages have been typically limited to lethargy, drowsiness, nausea, vomiting, and epigastric pain, which have been generally reversible with supportive care. Gastrointestinal bleeding has occurred. Hypertension, acute renal failure, respiratory depression, and coma have occurred, but were rare [see Warnings and Precautions (5.4, 5.5, 5.7)].

Manage patients with symptomatic and supportive care following an NSAID overdosage. There are no specific antidotes.

For additional information about overdosage treatment contact a poison control center (1-800-222-1222).

11 DESCRIPTION

COMBOGESIC IV (acetaminophen and ibuprofen) injection contains acetaminophen and ibuprofen, a nonsteroidal anti-inflammatory drug.

Acetaminophen chemical name is N-acetyl-p-aminophenol. Acetaminophen is a white, odorless, crystalline powder, possessing a slightly bitter taste. Acetaminophen is soluble in boiling water and 1N sodium hydroxide and is freely soluble in alcohol. Acetaminophen has a molecular weight of 151.16. The molecular formula is C8H9NO2 and the structural formula is:

Ibuprofen sodium dihydrate chemical name is 2-(4-isobutyl phenyl) propionic acid sodium salt dihydrate. Ibuprofen sodium dihydrate is a white powder. It has a molecular weight of 264.29. It is freely soluble in water. The molecular formula is C13H21NaO4 and the structural formula of ibuprofen sodium dihydrate is represented below:

COMBOGESIC IV injection is a sterile, clear, colorless, non-pyrogenic, isotonic solution, intended for intravenous infusion with a pH stability range of 6.3-7.3.

Each single-dose 100 mL vial contains 1,000 mg of acetaminophen and 300 mg of ibuprofen base (equivalent to 385 mg of ibuprofen sodium dihydrate), 25 mg of Cysteine hydrochloride monohydrate, 13 mg of Disodium phosphate dihydrate, 3,285 mg of Mannitol, Hydrochloric acid (for pH adjustment), Sodium hydroxide (for pH adjustment), Water for injection.

12 CLINICAL PHARMACOLOGY

12.1 Mechanism of Action

COMBOGESIC IV contains acetaminophen and ibuprofen as active drug substances.

Acetaminophen is a non-opiate, non-salicylate analgesic. The precise mechanism of the analgesic properties of acetaminophen is not established but is thought to primarily involve central actions. Ibuprofen is a nonsteroidal anti-inflammatory drug (NSAID). Its mechanism of action for analgesia, like that of other NSAIDs, is not completely understood, but involves inhibition of cyclooxygenase (COX-1 and COX-2).

Ibuprofen is a potent inhibitor of prostaglandin synthesis in vitro. Prostaglandins sensitize afferent nerves and potentiate the action of bradykinin in inducing pain in animal models. Prostaglandins are mediators of inflammation. Because ibuprofen is an inhibitor of prostaglandin synthesis, its mode of action may be due to a decrease of prostaglandins in peripheral tissues.

12.2 Pharmacodynamics

Hematological Effects

NSAIDs inhibit platelet aggregation and have been shown to prolong bleeding time in some patients. Unlike aspirin, their effect on platelet function is quantitatively less, of shorter duration, and reversible.

12.3 Pharmacokinetics

The pharmacokinetic profile of the intravenous formulation is dose proportional following the administration of a half dose and a full dose of COMBOGESIC IV.

The maximum concentration (Cmax) occurs at the end of the 15-min intravenous infusion of COMBOGESIC IV. While overall exposures (area under the concentration time curve [AUC]) were similar following a single dose of COMBOGESIC IV compared to the same dose given orally, the Cmax of the intravenous formulation was twice that of the oral formulation. As expected, the Tmax following intravenous administration was achieved much faster (in 15 minutes) than with the oral formulation. The mean Cmax and AUC0-inf of COMBOGESIC IV following administration of a single intravenous dose of 1,000 mg acetaminophen and 300 mg ibuprofen in adults were 34.30 mcg/mL and 56.48 mcg.h/mL for acetaminophen and 48.12 mcg/mL and 102.82 mcg.h/mL for ibuprofen, respectively.

A single-dose pharmacokinetic study of COMBOGESIC IV in healthy volunteers showed no drug interactions between acetaminophen and ibuprofen.

Distribution
Acetaminophen appears to be widely distributed throughout most body tissues except fat. Its apparent volume of distribution is about 0.9 L/kg. A relative small portion (~20%) of acetaminophen is bound to plasma protein.

Elimination
The half-life of acetaminophen is about 2 to 3 hours in adults. It is somewhat shorter in children and somewhat longer in neonates and in cirrhotic patients. Acetaminophen is eliminated from the body primarily by formation of glucuronide and sulfate conjugates in a dose-dependent manner. Ibuprofen is rapidly metabolized and eliminated in the urine. The serum half-life is 1.8 to 2.0 hours.

Metabolism
Acetaminophen is primarily metabolized in the liver by first-order kinetics and involves three principal separate pathways:
a) conjugation with glucuronide;
b) conjugation with sulfate; and
c) oxidation via the cytochrome, P450-dependent, mixed-function oxidase enzyme pathway to form a reactive intermediate metabolite, which conjugates with glutathione and is then further metabolized to form cysteine and mercapturic acid conjugates. The principal cytochrome P450 isoenzyme involved appears to be CYP2E1, with CYP1A2 and CYP3A4 as additional pathways.

In adults, the majority of acetaminophen is conjugated with glucuronic acid and, to a lesser extent, with sulfate. These glucuronide-, sulfate-, and glutathione-derived metabolites lack biologic activity. In premature infants, newborns, and young infants, the sulfate conjugate predominates.

Excretion
Less than 9% of acetaminophen is excreted unchanged in the urine.
The excretion of ibuprofen is virtually complete 24 hours after the last dose.
Studies have shown that following ingestion of the drug, 45% to 79% of the dose was recovered in the urine within 24 hours as metabolite A (25%), (+)-2-[p-(2hydroxymethyl-propyl) phenyl] propionic acid and metabolite B (37%), (+)-2-[p-(2carboxypropyl)phenyl]propionic acid; the percentages of free and conjugated ibuprofen were approximately 1% and 14%, respectively.

Specific Populations

Pediatric Patients
The pharmacokinetics of COMBOGESIC IV has not been studied in pediatric patients below 18 years of age.

Hepatic Impairment
The pharmacokinetics of COMBOGESIC IV in patients with impaired hepatic function has not been studied [see Warnings and Precautions (5.2) and Use in Specific Populations (8.6)].

Renal Impairment
The pharmacokinetics of COMBOGESIC IV in patients with renal impairment has not been studied. [see Warnings and Precautions (5.7) and Use in Specific Populations (8.7)].

Drug Interaction Studies
Aspirin: When NSAIDs were administered with aspirin, the protein binding of NSAIDs were reduced, although the clearance of free NSAID was not altered. The clinical significance of this interaction is not known. See Table 2 for clinically significant drug interactions of NSAIDs with aspirin [see Drug Interactions (7)].

13 NONCLINICAL TOXICOLOGY

13.1 Carcinogenesis, Mutagenesis, Impairment of Fertility

Carcinogenesis

Acetaminophen
Long-term studies in mice and rats have been completed by the National Toxicology Program to evaluate the carcinogenic potential of acetaminophen. In 2-year feeding studies, F344/N rats and B6C3F1 mice were fed a diet containing acetaminophen up to 6000 ppm. Female rats demonstrated equivocal evidence of carcinogenic activity based on increased incidences of mononuclear cell leukemia at 0.8 times the MHDD (based on a body surface area comparison). In contrast, there was no evidence of carcinogenic activity in male rats (0.7 times) or mice (1.2 - 1.4 times the MHDD, based on a body surface area comparison).

Ibuprofen
Adequate long-term animal studies have not been conducted to evaluate the carcinogenic potential of ibuprofen.

Mutagenesis

Acetaminophen
Acetaminophen was not mutagenic in the bacterial reverse mutation assay (Ames test). In contrast, acetaminophen tested positive in the in vitro mouse lymphoma assay and the in vitro chromosomal aberration assay using human lymphocytes.

In the published literature, acetaminophen has been reported to be clastogenic when administered a dose of 1,500 mg/kg/day to the rat model (at 3.6 times the MHDD, based on a body surface area comparison). In contrast, no clastogenicity was noted at a dose of 750 mg/kg/day (1.8 times the MHDD, based on a body surface area comparison), suggesting a threshold effect.

Ibuprofen
In published studies, ibuprofen was not mutagenic in the in vitro bacterial reverse mutation assay (Ames assay).

Impairment of Fertility

Acetaminophen
In studies conducted by the National Toxicology Program, fertility assessments with acetaminophen have been completed in Swiss mice via a continuous breeding study. There were no effects on fertility parameters in mice consuming up to approximately 1.1 times the MHDD of acetaminophen, (based on a body surface area comparison). Although there was no effect on sperm motility or sperm density in the epididymis, there was a significant increase in the percentage of abnormal sperm in mice consuming approximately 1.1 times the MHDD (based on a body surface area comparison) and there was a reduction in the number of mating pairs producing a fifth litter at this dose, suggesting the potential for cumulative toxicity with chronic administration of acetaminophen near the upper limit of daily dosing.

Published studies in rodents report that oral acetaminophen treatment of male animals at doses that are approximately 0.8 times the MHDD and greater (based on a body surface area comparison) result in decreased testicular weights, reduced spermatogenesis, and reduced fertility. Females given the same doses also showed reduced implantation sites. These effects appear to increase with the duration of treatment.

Published studies in rodents report that oral acetaminophen treatment of male animals at doses that are 1.2 times the MHDD and greater (based on a body surface area comparison) result in decreased testicular weights, reduced spermatogenesis, reduced fertility, and reduced implantation sites in females given the same doses. These effects appear to increase with the duration of treatment.

In a published mouse study, oral administration of 50 mg/kg acetaminophen to pregnant mice from Gestation Day 7 to delivery (0.06 times the MHDD) reduced the number of primordial follicles in female offspring and reduced the percentage of full-term pregnancies and number of pups born to these females exposed to acetaminophen in utero.

In a published study, pregnant rats oral administration of 350 mg/kg acetaminophen (0.85 times the MHDD) from Gestation Day 13 to 21 (dams), reduced the number of germ cells in the fetal ovary and decreased ovary weight and reduced number of pups per litter in F1 females as well as reduced ovary weights in F2 females.

Ibuprofen
In a published study, dietary administration of ibuprofen to male and female rats 8-weeks prior to and during mating at dose levels of 20 mg/kg (0.16-times the MRHD based on body surface area comparison) did not impact male or female fertility or litter size.

In other studies, adult mice were administered ibuprofen intraperitoneally at a dose of 5.6 mg/kg/day (0.023-times the MRHD based on body surface area comparison) for 35 or 60 days in males and 35 days in females. There was no effect on sperm motility or viability in males but decreased ovulation was reported in females.

14 CLINICAL STUDIES

14.1 Phase 3 Clinical Efficacy Study

COMBOGESIC IV was studied in a Phase 3, placebo-controlled, prospective, randomized, double-blind, parallel-design trial comparing the analgesic efficacy and safety of COMBOGESIC IV (n=75/276) with acetaminophen alone (n=75/276), ibuprofen alone (n=76/276) and placebo (n=50/276), after bunionectomy surgery. The demographic and baseline characteristics of the 276 eligible patients were balanced between the treatment groups with the majority of patients being female (82%) and white (62%) with a mean (SD) age of 42.4 (12.2) years.

The primary efficacy endpoint was the time-adjusted Sum of Pain Intensity Differences over 48 hours (SPID48) and analyzed with each pre-rescue Visual Analogue Scale (VAS) carried forward up to 2 hours. An analysis of covariance was used for the primary efficacy analysis with treatment as the fixed effect and baseline pain intensity score as the covariate on the intent to treat population.

The analysis of time-adjusted SPID48 demonstrated that COMBOGESIC IV (least square mean (LSM) = 36.7, standard error (SE) = 2.2) provided more effective pain relief than placebo (LSM = 17.5, SE = 2.7), acetaminophen (LSM = 19.3, SE = 2.2) or ibuprofen (LSM = 24.6, SE = 2.2).

Figure 1: Time-adjusted SPID48 with Pre-Rescue VAS Score Carried Forward up to 2 Hours

16 HOW SUPPLIED

COMBOGESIC IV (acetaminophen/ ibuprofen) injection 1,000 mg/300 mg per 100 mL (10 mg/3mg per mL): clear, colorless solution in single-dose vial. Discard unused portion.

NDC # 0143-9150-10: pack of 10 vials.

COMBOGESIC IV is a clear, colorless solution, free from visible particles.

Store at 20°C to 25°C (68°F to 77°F). Excursions permitted between 15°C to 30°C (59°F to 86°F) [See USP
Controlled Room Temperature].

Do not refrigerate or freeze. Store in the original carton in order to protect from light. Protect from heat.

17 PATIENT COUNSELING INFORMATION

Patients should be informed of the following information before initiating therapy with COMBOGESIC IV.

• Hepatotoxicity: Advise patients of the warning signs and symptoms of hepatotoxicity (e.g., nausea, fatigue, lethargy, pruritus, jaundice, right upper quadrant tenderness and "flu-like" symptoms). Advise patients to seek immediate medical assistance if these occur [see Warnings and Precautions (5.2)].

• Alcohol: Advise patients that COMBOGESIC IV should not be taken concomitantly with alcohol-containing beverages or other acetaminophen-containing products [see Warnings and Precautions (5.2)].

• Cardiovascular Thrombotic Events: Inform patients that COMBOGESIC IV, like other NSAID-containing medications, may cause serious CV side effects such as MI or stroke, which may result in hospitalization and even death. Advise patients to be alert for the signs and symptoms of cardiovascular thrombotic events including chest pain, shortness of breath, weakness, slurring of speech, and to report any of these symptoms to their health care provider immediately [see Warnings and Precautions (5.3)].

• Gastrointestinal Bleeding, Ulceration, and Perforation: Inform patients that COMBOGESIC IV, like other NSAID-containing medications, can cause GI discomfort and, rarely, serious GI side effects, such as ulcers and bleeding, which may result in hospitalization and even death. Advise patients to be alert for the signs and symptoms of ulcerations and bleeding, including epigastric pain, dyspepsia, melena, and hematemesis. In the setting of concomitant use of low-dose aspirin for cardiac prophylaxis, inform patients of the increased risk for and the signs and symptoms of GI bleeding [see Warnings and Precautions (5.4)].

• Heart Failure and Edema: Advise patients to be alert for the symptoms of congestive heart failure including shortness of breath, unexplained weight gain, or edema and to contact their healthcare provider if such symptoms occur [see Warnings and Precautions (5.6)].

• Weight Gain and Edema: Advise patients to promptly report unexplained weight gain or edema to their physicians [see Warnings and Precautions (5.6)].

• Hypersensitivity and Anaphylactic Reactions: Discontinue COMBOGESIC IV immediately if symptoms associated with allergy or hypersensitivity occur. Do not use COMBOGESIC IV in patients with known acetaminophen or ibuprofen allergy [see Warnings and Precautions (5.8 and 5.10)].

• Serious Skin Reactions, including DRESS: Advise patients to be alert for the signs and symptoms of skin rash and blisters, fever, or other signs of hypersensitivity such as itching, and to ask for medical advice when observing any indicative sign or symptoms [see Warnings and Precautions (5.8, 5.10, 5.11)].

• Female Fertility: Advise females of reproductive potential who desire pregnancy that NSAID containing products, including COMBOGESIC IV, may be associated with a reversible delay in ovulation [see Use in Specific Populations (8.3)].

• Fetal Toxicity: Inform pregnant women to avoid use of COMBOGESIC IV and other NSAIDs starting at 30 weeks gestation because of the risk of the premature closing of the fetal ductus arteriosus. If treatment with COMBOGESIC IV is needed for a pregnant woman between about 20 to 30 weeks gestation, advise her that she may need to be monitored for oligohydramnios, if treatment continues for longer than 48 hours [see Warnings and Precautions (5.12) and Use in Specific Populations (8.1)].

• Use of NSAIDs and Low-Dose Aspirin: Inform patients not to use low-dose aspirin concomitantly with COMBOGESIC IV until they talk to their healthcare provider [see Warnings and Precautions (5.4), see Drug Interactions (7)].

Manufactured by:
S.M. Farmaceutici SRL, Zona Industriale, 85050 Tito (PZ), Italy
Distributed by: Hikma Pharmaceuticals USA Inc.
Berkeley Heights, NJ 07922

Information and patents: https://www.combogesiciv.com

Revised: November 2024

PRINCIPAL DISPLAY PANEL

NDC 0143-9150-01 Rx only

KEEP OUT OF REACH OF CHILDREN

COMBOGESIC IV

(acetaminophen and ibuprofen) injection

1,000 mg/300 mg per 100 mL (10 mg/3 mg per mL)

For Intravenous Infusion Only

100 mL Single-Dose Vial. Discard unused portion.

NDC 0143-9150-10 Rx only

KEEP OUT OF REACH OF CHILDREN

COMBOGESIC IV

(acetaminophen and ibuprofen) injection

1,000 mg/300 mg per 100 mL (10 mg/3 mg per mL)

For Intravenous Infusion Only

Single-Dose Vial. Discard unused portion.

10 x 100 mL Vials